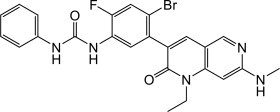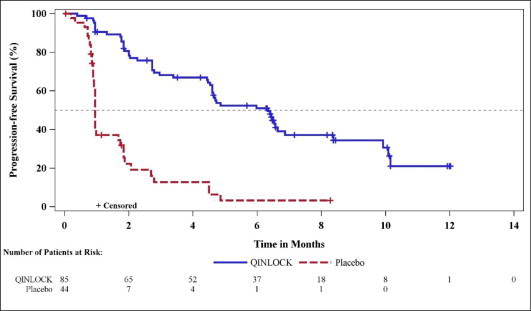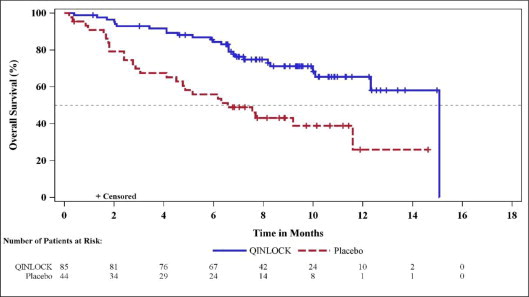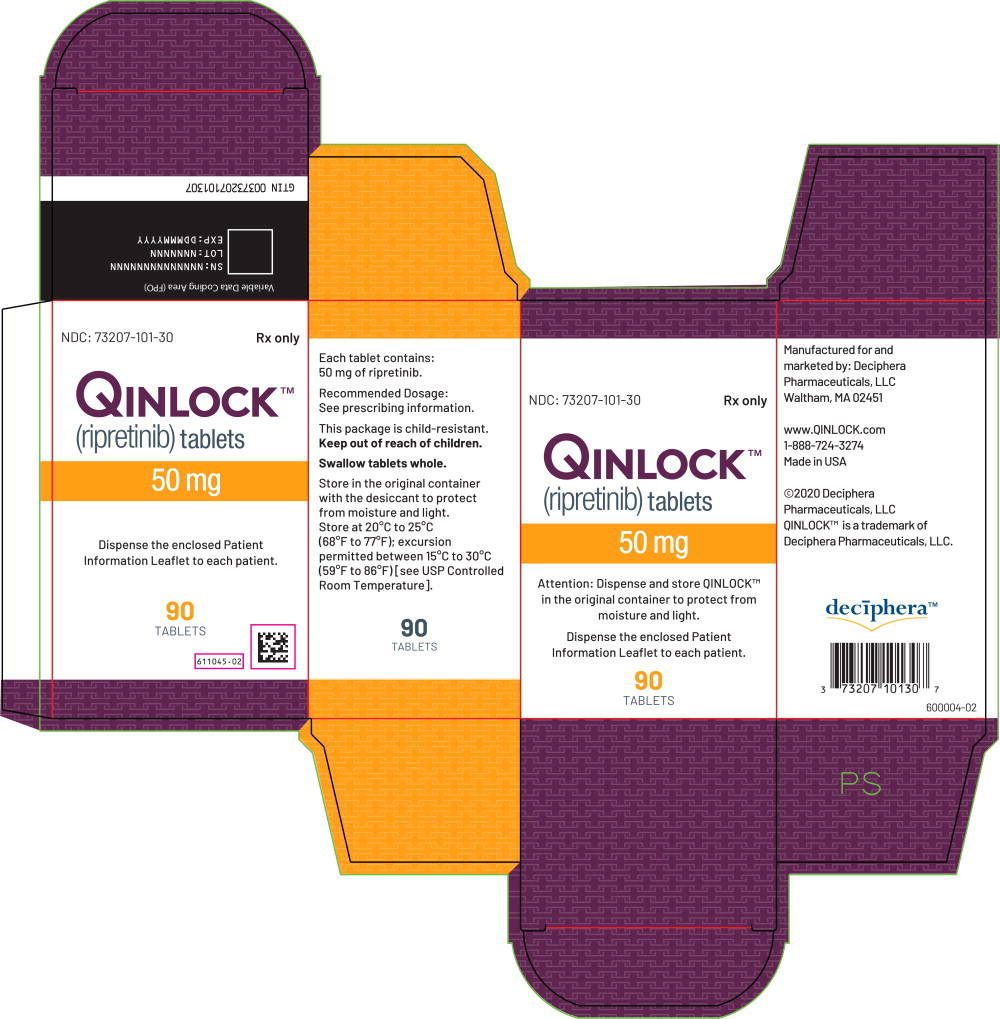 DRUG LABEL: QINLOCK

NDC: 73207-101 | Form: TABLET
Manufacturer: Deciphera Pharmaceuticals, LLC

Category: prescription | Type: HUMAN PRESCRIPTION DRUG LABEL
Date: 20250512

ACTIVE INGREDIENTS: Ripretinib
 50 mg/1 1
INACTIVE INGREDIENTS: hypromellose acetate succinate 06081224 (3 MM2/S); microcrystalline cellulose; lactose monohydrate; crospovidone; silicon dioxide; magnesium stearate

HIGHLIGHTS OF PRESCRIBING INFORMATION

These highlights do not include all the information needed to use QINLOCK safely and effectively. See full prescribing information for QINLOCK.
QINLOCK® (ripretinib) tablets, for oral use
Initial U.S. Approval: 2020

1 INDICATIONS AND USAGE

QINLOCK is a kinase inhibitor indicated for the treatment of adult patients with advanced gastrointestinal stromal tumor (GIST) who have received prior treatment with 3 or more kinase inhibitors, including imatinib. (1)

2 DOSAGE AND ADMINISTRATION

Recommended Dosage: 150 mg orally once daily with or without food. (2.1)

3 DOSAGE FORMS AND STRENGTHS

Tablets: 50 mg. (3)

4 CONTRAINDICATIONS

None. (4)

5 WARNINGS AND PRECAUTIONS

- Palmar-Plantar Erythrodysesthesia Syndrome: Based on severity, withhold QINLOCK and resume at same or reduced dose. (2.2, 5.1)
- New Primary Cutaneous Malignancies: Perform dermatologic evaluations when initiating QINLOCK and routinely during treatment. (5.2)
- Hypertension: Do not initiate QINLOCK in patients with uncontrolled hypertension and monitor blood pressure during treatment. Based on severity, withhold QINLOCK and then resume at same or reduced dose or permanently discontinue. (2.2, 5.3)
- Cardiac Dysfunction: Assess ejection fraction by echocardiogram or MUGA scan prior to initiating QINLOCK and during treatment, as clinically indicated. Permanently discontinue QINLOCK for Grade 3 or 4 left ventricular systolic dysfunction. (2.2, 5.4)
- Risk of Impaired Wound Healing: Withhold QINLOCK for at least 1 week prior to elective surgery. Do not administer for at least 2 weeks after major surgery and until adequate wound healing. The safety of resumption of QINLOCK after resolution of wound healing complications has not been established. (5.5)
- Photosensitivity: May cause photosensitivity reactions. Advise patients to limit direct ultraviolet exposure. (5.6)
- Embryo-Fetal Toxicity: Can cause fetal harm. Advise females of reproductive potential of the potential risk to a fetus and to use effective contraception. (5.7, 8.1, 8.3)

6 ADVERSE REACTIONS

The most common adverse reactions (≥20%) were alopecia, fatigue, nausea, abdominal pain, constipation, myalgia, diarrhea, decreased appetite, palmar-plantar erythrodysesthesia, and vomiting. The most common Grade 3 or 4 laboratory abnormalities (≥4%) were increased lipase and decreased phosphate. (6.1)

To report SUSPECTED ADVERSE REACTIONS, contact Deciphera Pharmaceuticals, LLC, at 1-888-724-3274 or FDA at 1-800-FDA-1088 or www.fda.gov/medwatch.

7 DRUG INTERACTIONS

- Strong CYP3A Inhibitors: Monitor more frequently for adverse reactions. (7.1)
- Strong CYP3A Inducers: Avoid concomitant use of strong CYP3A inducers. (7.1)
- Moderate CYP3A Inducers: Avoid concomitant use of moderate CYP3A inducers. If a moderate CYP inducer cannot be avoided, increase ripretinib dose frequency to twice daily. (2.3, 7.1)

8 USE IN SPECIFIC POPULATIONS

Lactation: Advise not to breastfeed. (8.2)

FULL PRESCRIBING INFORMATION

1 INDICATIONS AND USAGE

QINLOCK is indicated for the treatment of adult patients with advanced gastrointestinal stromal tumor (GIST) who have received prior treatment with 3 or more kinase inhibitors, including imatinib.

2 DOSAGE AND ADMINISTRATION

2.1 Recommended Dosage

The recommended dosage of QINLOCK is 150 mg orally once daily with or without food until disease progression or unacceptable toxicity.

Instruct patients to swallow tablets whole.

Advise patients to take QINLOCK at the same time each day.

Advise patients to take a missed dose if less than 8 hours have passed since the missed scheduled dose.

Advise patients not to take an additional dose if vomiting occurs after taking QINLOCK and to continue with their next scheduled dose.

2.2 Dosage Modifications for Adverse Reactions

The recommended dose reduction for adverse reactions is:

- QINLOCK 100 mg orally once daily.

Permanently discontinue QINLOCK in patients who are unable to tolerate 100 mg orally once daily.

The recommended dosage modifications of QINLOCK for adverse reactions are provided in Table 1.

Table 1: Recommended Dosage Modifications for QINLOCK for Adverse Reactions
Adverse Reaction | Severitya | QINLOCK Dosage Modifications
Palmar-Plantar Erythrodysesthesia Syndrome (PPES) [see Warnings and Precautions (5.1)] | Grade 2 | - Withhold QINLOCK until Grade ≤1 or baseline. If recovered within 7 days, resume QINLOCK at same dose; otherwise resume at reduced dose. - Consider re-escalating QINLOCK if maintained at Grade ≤1 or baseline for at least 28 days. - If PPES recurs, withhold QINLOCK until Grade ≤1 or baseline and then resume QINLOCK at a reduced dose regardless of time to improvement.
Palmar-Plantar Erythrodysesthesia Syndrome (PPES) [see Warnings and Precautions (5.1)] | Grade 3 | - Withhold QINLOCK for at least 7 days or until Grade ≤1 or baseline (maximum 28 days). Resume QINLOCK at a reduced dose. - Consider re-escalating QINLOCK if maintained at Grade ≤1 or baseline for at least 28 days.
Hypertension [see Warnings and Precautions (5.3)] | Grade 3 | - If symptomatic, withhold QINLOCK until symptoms have resolved and blood pressure is controlled. - If blood pressure is controlled to Grade ≤1 or baseline, resume QINLOCK at the same dose; otherwise, resume QINLOCK at reduced dose. - If Grade 3 hypertension recurs, withhold QINLOCK until symptoms have resolved and blood pressure is controlled. Resume QINLOCK at a reduced dose.
Hypertension [see Warnings and Precautions (5.3)] | Grade 4 | Permanently discontinue QINLOCK.
Left Ventricular Systolic Dysfunction [see Warnings and Precautions (5.4)] | Grade 3 or 4 | Permanently discontinue QINLOCK.
Arthralgia or Myalgia [see Adverse Reactions (6.1)] | Grade 2 | - Withhold QINLOCK until Grade ≤1 or baseline. If recovered within 7 days, resume QINLOCK at same dose; otherwise resume QINLOCK at reduced dose. - Consider re-escalating QINLOCK if maintained at Grade ≤1 or baseline for at least 28 days. - If arthralgia or myalgia recurs, withhold QINLOCK until Grade ≤1 or baseline and then resume QINLOCK at a reduced dose regardless of time to improvement.
Arthralgia or Myalgia [see Adverse Reactions (6.1)] | Grade 3 | - Withhold QINLOCK for at least 7 days or until Grade ≤1 or baseline (maximum of 28 days). Resume QINLOCK at a reduced dose. - Consider re-escalating QINLOCK if maintained at Grade ≤1 or baseline for at least 28 days.
Other Adverse Reactions [see Adverse Reactions (6.1)] | Grade 3 or 4 | - Withhold QINLOCK until Grade ≤1 or baseline (maximum 28 days), and then resume QINLOCK at a reduced dose; otherwise permanently discontinue. - Consider re-escalating QINLOCK if no recurrence of the adverse reaction for at least 28 days. - If Grade 3 or 4 recurs, permanently discontinue QINLOCK.
a Graded per National Cancer Institute Common Terminology Criteria for Adverse Events version 4.03 (NCI CTCAE v4.03).

2.3 Dose Modifications for Moderate CYP3A Inducers

Avoid concomitant use of moderate CYP3A inducers during QINLOCK treatment.

If a moderate CYP3A inducer cannot be avoided, increase the QINLOCK dosing frequency from the recommended dose of 150 mg once daily to 150 mg twice daily during the co-administration period. Monitor for clinical response and tolerability. If the concomitant moderate CYP3A inducer is discontinued, resume QINLOCK dosage back to 150 mg once daily 14 days after the discontinuation of the moderate CYP3A inducer [see Drug Interactions (7.1) and Clinical Pharmacology (12.3)].

For patients concomitantly using a moderate CYP3A inducer with QINLOCK (taking QINLOCK twice daily) who missed a dose:

- If less than 4 hours have passed since the missed scheduled dose, advise the patient to take the missed dose as soon as possible and then take the next dose at the regularly scheduled time.
- If more than 4 hours have passed since the missed scheduled dose, advise the patient to skip the missed dose and then take the next dose at the regularly scheduled time. [see Drug Interactions (7.1)].

3 DOSAGE FORMS AND STRENGTHS

Tablets: 50 mg, white to off-white, oval shaped, debossed with “DC1” on one side.

4 CONTRAINDICATIONS

None.

5 WARNINGS AND PRECAUTIONS

5.1 Palmar-Plantar Erythrodysesthesia Syndrome

In INVICTUS, Grade 1-2 palmar-plantar erythrodysesthesia syndrome (PPES) occurred in 21% of the 85 patients who received QINLOCK [see Adverse Reactions (6.1)]. PPES led to dose discontinuation in 1.2% of patients, dose interruption in 2.4% of patients, and dose reduction in 1.2% of patients.

Based on severity, withhold QINLOCK and then resume at same or reduced dose [see Dosage and Administration (2.2)].

5.2 New Primary Cutaneous Malignancies

In INVICTUS, cutaneous squamous cell carcinoma (cuSCC) occurred in 4.7% of the 85 patients who received QINLOCK, with a median time to event of 4.6 months (range: 3.8 to 6 months). In the pooled safety population, cuSCC and keratoacanthoma occurred in 7% and 1.9% of patients, respectively.

In INVICTUS, melanoma occurred in 2.4% of the 85 of patients who received QINLOCK. In the pooled safety population, melanoma occurred in 0.9% of patients.

Perform dermatologic evaluations when initiating QINLOCK and routinely during treatment. Manage suspicious skin lesions with excision and dermatopathologic evaluation. Continue QINLOCK at the same dose.

5.3 Hypertension

In INVICTUS, Grade 1-3 hypertension occurred in 14% of the 85 patients who received QINLOCK, including Grade 3 hypertension in 7% [see Adverse Reactions (6.1)].

Do not initiate QINLOCK in patients with uncontrolled hypertension. Adequately control blood pressure prior to initiating QINLOCK. Monitor blood pressure as clinically indicated during treatment with QINLOCK, and initiate or adjust antihypertensive therapy as appropriate. Based on severity, withhold QINLOCK and then resume at same or reduced dose or permanently discontinue [see Dosage and Administration (2.2)].

5.4 Cardiac Dysfunction

In INVICTUS, cardiac failure occurred in 1.2% of the 85 patients who received QINLOCK. In the pooled safety population, cardiac dysfunction (including cardiac failure, acute left ventricular failure, diastolic dysfunction, and ventricular hypertrophy) occurred in 1.7% of patients, including Grade 3 adverse reactions in 1.1%.

In INVICTUS, Grade 3 decreased ejection fraction occurred in 1.3% of the 77 patients who received QINLOCK and who had a baseline and at least one post-baseline echocardiogram. In the pooled safety population, Grade 3 decreased ejection fraction occurred in 1.9% of the 263 patients who received QINLOCK and who had a baseline and at least one post-baseline echocardiogram.

In INVICTUS, cardiac dysfunction led to dose discontinuation in 1.2% of the 85 patients who received QINLOCK. The safety of QINLOCK has not been assessed in patients with a baseline ejection fraction below 50%.

Assess ejection fraction by echocardiogram or MUGA scan prior to initiating QINLOCK and during treatment, as clinically indicated. Permanently discontinue QINLOCK for Grade 3 or 4 left ventricular systolic dysfunction [see Dosage and Administration (2.2)].

5.5 Risk of Impaired Wound Healing

Impaired wound healing complications can occur in patients who receive drugs that inhibit the vascular endothelial growth factor (VEGF) signaling pathway. Therefore, QINLOCK has the potential to adversely affect wound healing.

Withhold QINLOCK for at least 1 week prior to elective surgery. Do not administer for at least 2 weeks following major surgery and until adequate wound healing. The safety of resumption of QINLOCK after resolution of wound healing complications has not been established.

5.6 Photosensitivity

QINLOCK may cause photosensitivity reactions. In all patients treated with QINLOCK in clinical trials (n=621), photosensitivity reactions occurred in 0.6% of patients.

Advise patients to limit direct ultraviolet exposure during treatment with QINLOCK and for at least one week after discontinuation of treatment.

5.7 Embryo-Fetal Toxicity

Based on findings from animal studies and its mechanism of action, QINLOCK can cause fetal harm when administered to a pregnant woman. Oral administration of ripretinib to pregnant rats and rabbits during the period of organogenesis resulted in malformations primarily associated with the cardiovascular and skeletal systems, anatomic variations, decreased fetal body weight, and increased post-implantation loss at exposures approximately one half of the recommended dose of 150 mg once daily based on area under the curve (AUC).

Advise pregnant women of the potential risk to a fetus. Advise females of reproductive potential to use effective contraception during treatment with QINLOCK and for 1 week after the last dose. Advise males with female partners of reproductive potential to use effective contraception during treatment with QINLOCK and for 1 week after the last dose [see Use in Specific Populations (8.1, 8.3), Nonclinical Toxicology (13.1)].

6 ADVERSE REACTIONS

The following clinically significant adverse reactions are discussed elsewhere in the labeling:

- Palmar-Plantar Erythrodysesthesia Syndrome [see Warnings and Precautions (5.1)]
- New Primary Cutaneous Malignancies [see Warnings and Precautions (5.2)]
- Hypertension [see Warnings and Precautions (5.3)]
- Cardiac Dysfunction [see Warnings and Precautions (5.4)]
- Photosensitivity [see Warnings and Precautions (5.6)]

6.1 Clinical Trials Experience

Because clinical trials are conducted under widely varying conditions, adverse reaction rates observed in the clinical trials of a drug cannot be directly compared to rates in the clinical trials of another drug and may not reflect the rates observed in practice.

Unless otherwise specified, the pooled safety population described in the WARNINGS AND PRECAUTIONS reflect exposure to QINLOCK as a single agent in 351 patients with advanced solid tumors enrolled in either an open-label dose finding with cohort expansion trial or INVICTUS. Among the patients who received QINLOCK in these trials, 52% were exposed for 6 months or longer and 21% were exposed for greater than one year.

Gastrointestinal Stromal Tumor

Patients Who Received Prior Treatment with Imatinib, Sunitinib and Regorafenib

The safety of QINLOCK was evaluated in INVICTUS [see Clinical Studies (14)]. Patients received QINLOCK 150 mg taken orally once daily (n=85) or placebo (n=43). Among the patients who received QINLOCK, 46% were exposed for 6 months or longer and 3.5% were exposed for greater than one year.

Serious adverse reactions occurred in 31% of patients who received QINLOCK. Serious adverse reactions that occurred in >2% of patients were abdominal pain (4.7%), anemia (3.5%), nausea (2.4%), and vomiting (2.4%).

Permanent discontinuation due to an adverse reaction occurred in 8% of patients who received QINLOCK. Adverse reactions resulting in permanent discontinuation in ≥1% of patients included general physical health deterioration (2.4%), anemia (1.2%), cardiac failure (1.2%), PPES (1.2%), and vomiting (1.2%).

Dosage interruptions due to an adverse reaction occurred in 24% of patients who received QINLOCK. Adverse reactions requiring dosage interruption in >2% of patients included nausea (3.5%), increased blood bilirubin (2.4%), and PPES (2.4%).

Dose reductions due to an adverse reaction occurred in 7% of patients who received QINLOCK. Adverse reactions resulting in a dose reduction in ≥1.2% of patients were abdominal pain, agitation, alopecia, arthritis, dermatosis, gastrointestinal disorder, hyperesthesia, myalgia, PPES, and decreased weight.

The most common adverse reactions (≥20%), were alopecia, fatigue, nausea, abdominal pain, constipation, myalgia, diarrhea, decreased appetite, PPES, and vomiting. The most common Grade 3 or 4 laboratory abnormalities (≥4%) were increased lipase and decreased phosphate.

Table 2 summarizes the adverse reactions in INVICTUS.

Table 2: Adverse Reactions (≥10%) in Patients with Gastrointestinal Stromal Tumor Who Received QINLOCK in INVICTUS
Adverse Reaction | QINLOCK (N=85) |  | Placebo (N=43)
Adverse Reaction | Grades 1-4 | Grades 3-4 | Grades 1-4 | Grades 3-4
Skin and subcutaneous tissue
Alopecia | 52 | 0 | 4.7 | 0
Palmar-plantar erythrodysesthesia syndrome | 21 | 0 | 0 | 0
Dry skin | 13 | 0 | 7 | 0
Pruritus | 11 | 0 | 4.7 | 0
General
Fatigue | 42 | 3.5 | 23 | 2.3
Peripheral edema | 17 | 1.2 | 7 | 0
Asthenia | 13 | 1.2 | 14 | 4.7
Gastrointestinal
Nausea | 39 | 3.5 | 12 | 0
Abdominal pain | 36 | 7 | 30 | 4.7
Constipation | 34 | 1.2 | 19 | 0
Diarrhea | 28 | 1.2 | 14 | 2.3
Vomiting | 21 | 3.5 | 7 | 0
Stomatitis | 11 | 0 | 0 | 0
Musculoskeletal and connective tissue
Myalgia | 32 | 1.2 | 12 | 0
Arthralgia | 18 | 0 | 4.7 | 0
Muscle spasms | 15 | 0 | 4.7 | 0
Metabolism and nutrition
Decreased appetite | 27 | 1.2 | 21 | 2.3
Investigations
Decreased weight | 19 | 0 | 12 | 0
Nervous system
Headache | 19 | 0 | 4.7 | 0
Vascular
Hypertension | 14 | 7 | 4.7 | 0
Respiratory, thoracic and mediastinal
Dyspnea | 13 | 0 | 0 | 0

Table 3 summarizes the laboratory abnormalities in INVICTUS.

Table 3: Select Laboratory Abnormalities (≥10%) Worsening from Baseline in Patients with Gastrointestinal Stromal Tumor Who Received QINLOCK with a Difference Between Arms of >5% Compared to Placebo in INVICTUS
Laboratory Abnormality | QINLOCKa (N=85) |  | Placeboa (N=43)
Laboratory Abnormality | Grades 1-4 | Grades 3-4 b | Grades 1-4 | Grades 3-4
Hematology
Increased activated partial thromboplastin time | 35 | 0 | 9 | 0
Increased INR | 21 | 3.8 | 15 | 0
Decreased neutrophil count | 10 | 0 | 2.5 | 0
Chemistry
Increased lipase | 32 | 7 | 13 | 8
Decreased phosphate | 26 | 4.9 | 2.5 | 0
Increased triglycerides | 26 | 2.4 | 23 | 0
Decreased calcium | 23 | 0 | 8 | 0
Increased blood bilirubin | 22 | 0 | 5 | 2.5
Increased CPK | 21 | 1.2 | 10 | 0
Decreased sodium | 17 | 2.4 | 10 | 2.5
Increased creatinine | 16 | 0 | 18 | 0
Increased serum amylase | 13 | 1.2 | 5 | 0
Increased ALT | 12 | 1.2 | 5 | 0
CPK=creatine phosphokinase; INR=international normalized ratio; AST=aspartate aminotransferase; ALT=alanine aminotransferase
a. The denominator used to calculate the rate varied from 82 to 83 for QINLOCK and 34 to 40 for placebo based on the number of patients with a baseline value and at least one post-treatment value.
b. Only includes Grade 3 laboratory abnormalities.

Other Adverse Reactions

Clinically relevant adverse reactions that occurred in <10% of QINLOCK-treated patients in INVICTUS included peripheral sensory neuropathy, dermatitis acneiform, and rash.

Clinically relevant adverse reactions that occurred in <10% of patients in the pooled safety population included cardiac ischemic events (including acute coronary syndrome and fatal cardiac arrest or myocardial infarction). Photosensitivity occurred in 0.6% [see Warnings and Precautions (5.6)].

7 DRUG INTERACTIONS

7.1 Effect of Other Drugs on QINLOCK

Table 4 includes drug interactions that affect the pharmacokinetics of ripretinib.

Table 4: Drug Interactions that Affect QINLOCK
Strong CYP3A Inhibitors
Clinical Impact | - Coadministration of QINLOCK with a strong CYP3A inhibitor increased the exposure of ripretinib and its active metabolite (DP-5439), which may increase the risk of adverse reactions [see Clinical Pharmacology (12.3)].
Prevention or Management | - Monitor patients more frequently for adverse reactions.
Strong and Moderate CYP3A Inducers
Clinical Impact | - Coadministration of QINLOCK with a strong CYP3A inducer decreased the exposure of ripretinib and its active metabolite (DP-5439), which may decrease QINLOCK anti-tumor activity [see Clinical Pharmacology (12.3)]. - Coadministration of QINLOCK with moderate CYP3A inducers is predicted to decrease the exposure of ripretinib and its active metabolite (DP-5439), which may decrease QINLOCK anti-tumor activity [see Clinical Pharmacology (12.3)].
Prevention or Management | - Avoid concomitant use of QINLOCK with strong CYP3A inducers. - Avoid concomitant use of QINLOCK with moderate CYP3A inducers. If a moderate CYP3A inducer cannot be avoided, increase QINLOCK dosing frequency from the recommended dose of 150 mg once daily to 150 mg twice daily during the co-administration period. Monitor for clinical response and tolerability [see Dosage and Administration (2.3)].

8 USE IN SPECIFIC POPULATIONS

8.1 Pregnancy

Risk Summary

Based on findings from animal studies and its mechanism of action [see Clinical Pharmacology (12.1)], QINLOCK can cause fetal harm when administered to a pregnant woman. There are no available data on the use of QINLOCK in pregnant women to inform a drug-associated risk. Administration of ripretinib to pregnant rats and rabbits during the period of organogenesis resulted in malformations primarily associated with the cardiovascular and skeletal systems, anatomic variations, reduced fetal body weight, and increased post-implantation loss at maternal exposures that were approximately equal to the human exposure at the recommended dose of 150 mg (see Data). Advise pregnant women of the potential risk to a fetus.

In the U.S. general population, the estimated background risk of major birth defects and miscarriage in clinically recognized pregnancies is 2 to 4% and 15 to 20%, respectively.

Data

Animal Data

In an embryo-fetal development study investigating daily doses of ripretinib administered during the period of organogenesis in rats, ripretinib resulted in malformations primarily associated with the cardiovascular and skeletal systems, including interrupted or retroesophageal aortic arch and retroesophageal subclavian artery, fusion of the exoccipital bone to the first cervical vertebra, branched and fused ribs, anomalies of the cervical, thoracic, caudal, and sacral vertebrae, absent forepaw phalanges, and absent metacarpals at a dose of 20 mg/kg/day (approximately one half of the human exposure at the recommended dose of 150 mg). An increased incidence of anatomic variations were also observed at 20 mg/kg/day. Variations included malpositioned carotid and subclavian artery origins, malpositioned subclavian artery, absent or elongated innominate artery, misshapen and nodulated ribs, bipartite, incompletely ossified, or unossified vertebral centra, small or misshapen vertebral arches, and reductions in ossified forelimb and hindlimb phalanges, hindlimb metatarsals, and caudal vertebrae.

In a preliminary embryo-fetal development study investigating the administration of ripretinib in rabbits during the period of organogenesis, ripretinib resulted in total loss of pregnancy at doses of 150 mg/kg (approximately 3.5 times the human exposure at the recommended dose of 150 mg). At a dose of 40 mg/kg (approximately 2.1 times the human exposure at the recommended dose of 150 mg), toxicities included increased post-implantation loss and decreased fetal body weights.

8.2 Lactation

Risk Summary

There are no data regarding the presence of ripretinib or its metabolites in either human milk or its effects on a breastfed child or on milk production. Because of the potential for serious adverse reactions in the breastfed child, advise women not to breastfeed during treatment with QINLOCK and for 1 week after the last dose.

8.3 Females and Males of Reproductive Potential

QINLOCK can cause fetal harm when administered to a pregnant woman [see Use in Specific Populations (8.1)].

Pregnancy Testing

Verify pregnancy status of females of reproductive potential prior to the initiation of QINLOCK [see Use in Specific Populations (8.1)].

Contraception

Females

Advise females of reproductive potential to use effective contraception during treatment and for 1 week after the last dose.

Males

Advise males with female partners of reproductive potential to use effective contraception during treatment and for 1 week after the last dose.

Infertility

Based on findings from animal studies, QINLOCK may impair fertility in males of reproductive potential [see Nonclinical Toxicology (13.1)].

8.4 Pediatric Use

The safety and effectiveness of QINLOCK in pediatric patients have not been established.

Animal Toxicity Data

In 13-week repeat-dose studies in rats there were dose-dependent findings of increased osteoblastic surface and decreased trabeculae of the femur at doses ≥30 mg/kg/day (approximately one half of the human exposure at the recommended dose of 150 mg). There were additional findings of missing or discolored teeth that were accompanied by dose-dependent incisor degeneration at doses ≥30 mg/kg/day.

8.5 Geriatric Use

Of the 85 patients in INVICTUS who received QINLOCK 150 mg orally once daily, 24% were between 65 to 74 years of age and 9% were 75 years of age or older. Clinical studies of QINLOCK did not include sufficient numbers of patients aged 65 and older to determine whether they respond differently from younger patients.

8.6 Hepatic Impairment

No dose adjustment is recommended in patients with hepatic impairment (Child-Pugh A, B, or C) [see Clinical Pharmacology (12.3)].

11 DESCRIPTION

Ripretinib is a kinase inhibitor. The chemical name of ripretinib is 1-(4-bromo-5-[1-ethyl-7-(methylamino)-2-oxo-1,2-dihydro-1,6-naphthyridin-3-yl]-2-fluorophenyl)-3-phenylurea. The molecular formula is C24H21BrFN5O2 and the molecular weight is 510.36 g/mol. The chemical structure of ripretinib is shown below:

Ripretinib is a white to off-white crystalline solid. Ripretinib is a lipophilic, weak base, and practically insoluble in aqueous media.

QINLOCK is available as a white to off-white, oval tablets for oral use containing 50 mg of ripretinib. The tablet is debossed with “DC1” on one side. Each tablet contains the following inactive ingredients: crospovidone, hypromellose acetate succinate, lactose monohydrate, magnesium stearate, microcrystalline cellulose, and silicon dioxide.

12 CLINICAL PHARMACOLOGY

12.1 Mechanism of Action

Ripretinib is a tyrosine kinase inhibitor that inhibits KIT proto-oncogene receptor tyrosine kinase (KIT) and platelet derived growth factor receptor A (PDGFRA) kinase, including wild type, primary, and secondary mutations. Ripretinib also inhibits other kinases in vitro, such as PDGFRB, TIE2, VEGFR2, and BRAF.

12.2 Pharmacodynamics

Exposure-Response Relationships

Ripretinib exposure-response relationships and the time course of pharmacodynamics have not been fully characterized.

Cardiac Electrophysiology

No large mean increase in QTc interval (i.e. >20 ms) was detected following treatment with QINLOCK at the recommended dose of 150 mg taken orally once daily.

12.3 Pharmacokinetics

The pharmacokinetics of ripretinib and its equally active metabolite (DP-5439) were characterized in clinical studies. In patients with advanced malignancies, ripretinib AUC0-24h increased proportionally over a dose range of 20-250 mg (0.13 to 1.67 times the recommended dose), but Cmax was less than dose proportional; DP-5439 Cmax and AUC0-24h were less than dose proportional within the dose range of 50-250 mg (0.33 to 1.67 times the recommended dose).

No clinically significant differences in the Cmax and AUC0-24h were observed between administration of QINLOCK with a high-fat meal (150, 250, and 500-600 calories from protein, carbohydrate, and fat, respectively) and under fasted conditions. The pharmacokinetic parameters of ripretinib and DP-5439 are summarized in Table 5.

Table 5: Pharmacokinetic Parameters of Ripretinib and DP-5439
Parameter |  | Ripretinib | DP-5439
General Information
Steady state exposure following QINLOCK 150 mg once daily [Mean (CV%)] | Cmax (ng/mL) | 761 (32) | 804 (46)
Steady state exposure following QINLOCK 150 mg once daily [Mean (CV%)] | AUC0-12h (ng•h/mL) | 5678 (32) | 7138 (44)
Time to steady state [Days] |  | 14 | 14
Accumulation ratio (AUC0-12h) [Mean (CV%)]a |  | 1.7 (55) | 5.29 (49)
Absorption
Tmax [Median in hours]b |  | 4 | 15.6
Distribution
Plasma protein binding (in vitro) | Human serum albumin | 99.8% | 99.7%
Plasma protein binding (in vitro) | α-1 acid glycoprotein | 99.4% | >99.8%
Steady state apparent volume of distribution, L [Mean (CV%)]b |  | 307 (39) | 507 (51)
Elimination
Apparent clearance, L/hr [Mean (CV%)]b |  | 15.3 (45) | 17.5 (63)
Half-life, hours [Mean (CV%)]b |  | 14.8 (30) | 17.8 (23)
Metabolism
Metabolic pathways | Major | CYP3A4 | CYP3A4
Metabolic pathways | Minor | CYP2C8 and CYP2D6 | CYP2C8, CYP2E1 and CYP2D6
Excretion
Excretion pathways | Feces | 34% | 6%
Excretion pathways | Urine | 0.02% | 0.1%
a. Estimated based on cycle 1, day 15
b. After a single oral dose of 150 mg
CV=coefficient of variation; Cmax=maximum plasma concentration; AUC0-12h=area under the plasma concentration-time curve from time zero to 12 hours; AUC0-24h=area under the plasma concentration-time curve from time zero to 24 hours; Tmax=time to maximum concentration

Specific Populations

No clinically significant differences in the pharmacokinetics of ripretinib were observed based on age (19 to 87 years), sex, race (White, Black, and Asian), body weight (39 to 138 kg), tumor (GIST or other solid tumors), prior gastrectomy, mild to moderate renal impairment (CLcr 30 to <90 mL/min estimated by Cockcroft-Gault), and mild hepatic impairment (total bilirubin ≤ULN and AST >ULN or total bilirubin 1 to 1.5 × ULN and AST any).

The effects of severe renal impairment (CLcr 15 to 29 mL/min) on the pharmacokinetics of ripretinib have not been studied.

Patients with Hepatic Impairment

In subjects with mild hepatic impairment, there were no clinically significant changes in AUC0-last and Cmax when compared to matched healthy subjects.

In subjects with moderate hepatic impairment, ripretinib AUC0-last increased 2-fold while Cmax was unchanged when compared to matched healthy subjects. The combined AUC0-last of ripretinib and DP-5439 increased 1.5-fold.

In subjects with severe hepatic impairment, ripretinib AUC0-last increased 2.6-fold and Cmax decreased by 24% when compared to matched healthy subjects. The combined AUC0-last of ripretinib and DP-5439 increased by 1.4-fold.

The observed magnitude of increase in ripretinib and the combination of ripretinib and DP-5439 exposures in subjects with hepatic impairment is unlikely to be clinically relevant based on the known safety profile of ripretinib.

Drug Interaction Studies

Clinical Studies and Model-Informed Approaches

CYP Enzymes: No clinically significant differences in the pharmacokinetics of repaglinide (a sensitive substrate for CYP2C8) were observed when used concomitantly with QINLOCK.

Strong CYP3A Inhibitors: Coadministration of QINLOCK with itraconazole (a strong CYP3A inhibitor and also a P-gp inhibitor) increased ripretinib Cmax by 36% and AUC0-inf by 99% and also increased DP-5439 AUC0-inf by 99% with no change in its Cmax.

Strong CYP3A Inducers: Coadministration of QINLOCK with rifampin (a strong CYP3A inducer) decreased ripretinib Cmax by 18% and AUC0-inf by 61% and also decreased DP-5439 AUC0-inf by 57% with increased Cmax by 37%.

Moderate CYP3A Inducers: Coadministration of QINLOCK with efavirenz (a moderate CYP3A inducer) was predicted to decrease ripretinib Cmax by 24% and decrease AUC0-inf by 56%.

Proton Pump Inhibitors: No clinically significant differences in the plasma exposure to ripretinib and DP-5439 were observed when QINLOCK was coadministered with pantoprazole (a proton pump inhibitor).

In Vitro Studies

CYP Enzymes: Ripretinib and DP-5439 are not inducers of CYP1A2, CYP2B6, or CYP3A4.

Transporter Systems: Ripretinib and DP-5439 are substrates for P-glycoprotein (P-gp) and Breast Cancer Resistance Protein (BCRP). Ripretinib is an inhibitor of P-gp and BCRP. DP-5439 is an inhibitor of BCRP and Multidrug And Toxin Extrusion Protein 1 (MATE1).

UGT1A Substrates: Ripretinib is an inhibitor of UGT1A1, UGT1A3, UGT1A4, UGT1A7, and UGT1A8.

13 NONCLINICAL TOXICOLOGY

13.1 Carcinogenesis, Mutagenesis, Impairment of Fertility

Carcinogenicity studies have not been conducted with ripretinib.

Ripretinib was not mutagenic in an in vitro bacterial reverse mutation (Ames) assay or clastogenic in either an in vitro human lymphocyte culture micronucleus assay or an in vivo rat bone marrow micronucleus assay.

Dedicated fertility studies in male animals were not conducted with ripretinib. Findings in male reproductive organs occurred in repeat-dose toxicity studies and included degeneration of the testes and cellular debris of the epididymis in males administered ≥30 mg/kg/day (approximately one half of the human exposure at the recommended dose of 150 mg).

14 CLINICAL STUDIES

The efficacy of QINLOCK was evaluated in INVICTUS, an international, multi-center, randomized (2:1), double-blind, placebo-controlled trial (NCT03353753). Eligible patients had unresectable, locally advanced or metastatic gastrointestinal stromal tumor (GIST) and had received prior treatment with imatinib, sunitinib, and regorafenib. Randomization was stratified by prior lines of therapy (3 versus ≥4) and Eastern Cooperative Oncology Group (ECOG) performance status (0 versus 1 or 2). Patients received QINLOCK 150 mg or placebo orally once daily until disease progression or unacceptable toxicity. Tumor response assessments were performed every 28 days through for the first 4 months and then every 56 days thereafter. The major efficacy outcome measure was progression-free survival (PFS) based on disease assessment by blinded independent central review (BICR) using modified RECIST 1.1 criteria, in which lymph nodes and bone lesions were not target lesions and a progressively growing new tumor nodule within a pre-existing tumor mass must meet specific criteria to be considered unequivocal evidence of progression. Additional efficacy outcome measures included objective response rate (ORR) by BICR and overall survival (OS). Patients randomized to receive placebo could be treated with QINLOCK at the time of disease progression.

A total of 129 patients were randomized, 85 to QINLOCK and 44 to placebo.

Patient characteristics of the intent-to-treat (ITT) population in INVICTUS were median age of 60 years (range: 29 to 83 years), with 39% aged ≥65 years; 57% were male; 75% were White; and 92% had an ECOG performance status of 0 or 1. Sixty-three percent (63%) of patients received 3 prior therapies and 37% received 4 or more prior therapies. Sixty-six percent (66%) of patients randomized to placebo switched to QINLOCK after disease progression.

Efficacy results from INVICTUS are summarized in Table 6.

Table 6: Efficacy Results of INVICTUS
 | QINLOCK (N=85) | Placebo (N=44)
Progression-Free Survivala
Number of events (%) | 51 (60) | 37 (84)
Progressive disease | 46 (54) | 32 (73)
Deaths | 5 (6) | 5 (11)
Median PFS (months) (95% CI) | 6.3 (4.6, 6.9) | 1.0 (0.9, 1.7)
Hazard ratio (95% CI)c | 0.15 (0.09, 0.25)
p-valueb | < 0.0001
Overall Response Ratea
Overall Response Rate (%) | 9 | 0
(95% CI) | (4.2, 18) | (0, 8)
p-valued | 0.0504
Overall Survival e
Number of deaths (%) | 26 (31) | 26 (59)
Median OS (months) (95% CI) | 15.1 (12.3, 15.1) | 6.6 (4.1, 11.6)
Hazard ratio (95% CI)c | 0.36 (0.21, 0.62)
BICR=Blinded Independent Central Review; CI=Confidence Interval
a. Assessed per BICR.
b. p-value is based on 2-sided stratified log-rank test.
c. Hazard ratio is based on Cox proportional regression model. This model includes treatment and randomization stratification factors as fixed factors.
d. Based on Fisher's exact test. The p-value is not statistically significant.
e. Not evaluated for statistical significance as a result of the sequential testing procedure for the secondary endpoints of ORR and OS.

Figure 1: Kaplan-Meier Curve of Progression-Free Survival in INVICTUS

Figure 2: Kaplan-Meier Curve of Overall Survival in INVICTUS

16 HOW SUPPLIED/STORAGE AND HANDLING

QINLOCK 50 mg tablets are white to off-white, oval shaped, and debossed with “DC1” on one side.

90-count bottles NDC 73207-101-30

Dispense in original container only. Store in the original container with the desiccant to protect from moisture and light. Replace cap securely each time after opening. Do not discard desiccant.

Store at 20°C to 25°C (68°F to 77°F); excursion permitted between 15°C to 30°C (59°F to 86°F) [see USP Controlled Room Temperature].

17 PATIENT COUNSELING INFORMATION

Advise the patient to read the FDA-approved patient labeling (Patient Information).

Palmar-Plantar Erythrodysesthesia Syndrome

Advise patients to contact their healthcare provider immediately if they experience severe skin changes [see Warnings and Precautions (5.1)].

New Primary Cutaneous Malignancies

Advise patients to contact their healthcare provider immediately for change in or development of new skin lesions [see Warnings and Precautions (5.2)].

Hypertension

Advise patients that hypertension may develop during treatment with QINLOCK and that blood pressure should be monitored regularly during treatment [see Warnings and Precautions (5.3)].

Cardiac Dysfunction

Advise patients that cardiac failure may develop during treatment with QINLOCK and that signs or symptoms of cardiac failure should be regularly monitored during treatment. Advise patients to contact their healthcare provider immediately for signs or symptoms of cardiac dysfunction [see Warnings and Precautions (5.4)].

Risk of Impaired Wound Healing

Advise patients that QINLOCK may impair wound healing. Advise patients to inform their healthcare provider of any planned surgical procedure [see Warnings and Precautions (5.5)].

Photosensitivity

Inform patients that there is a potential risk of photosensitivity reactions with QINLOCK. Advise patients to limit direct ultraviolet exposure by using sunscreen and protective clothing during treatment with QINLOCK [see Warnings and Precautions (5.6)].

Embryo-Fetal Toxicity

- Advise pregnant women and females of reproductive potential of the potential risk to a fetus. Advise females of reproductive potential to inform their healthcare provider of a known or suspected pregnancy [see Warnings and Precautions (5.7), Use in Specific Populations (8.1)].
- Advise females of reproductive potential to use effective contraception during treatment with QINLOCK and for 1 week after the last dose [see Use in Specific Populations (8.3)].
- Advise males with female partners of reproductive potential to use effective contraception during treatment with QINLOCK and for 1 week after the last dose [see Use in Specific Populations (8.3), Nonclinical Toxicology (13.1)].

Lactation

Advise females not to breastfeed during treatment with QINLOCK and for 1 week after the last dose [see Use in Specific Populations (8.2)].

Infertility

Advise males of reproductive potential that QINLOCK may impair fertility [see Use in Specific Populations (8.3), Nonclinical Toxicology (13.1)].

Drug Interactions

Advise patients to inform their healthcare provider of all concomitant medications, including prescription medicines, over-the-counter drugs, vitamins, and herbal products [see Drug Interactions (7.1)].

Dosage and Administration

Instruct patients to take QINLOCK at the same time each day (once daily) with or without food. Advise patients to swallow tablets whole. Inform patients about what to do in the event they miss a dose or vomit after taking a dose of QINLOCK [see Dosage and Administration (2.1)].

Storage Instructions

Store QINLOCK in the original container at room temperature between 20ºC to 25ºC (68ºF to 77ºF).

Manufactured for and marketed by:
Deciphera Pharmaceuticals, LLC
200 Smith Street, Waltham, MA 02451

Patient Information
QINLOCK® (kin-lok)
(ripretinib)
tablets

What is QINLOCK?
QINLOCK is a prescription medicine used to treat adults with advanced gastrointestinal stromal tumor (GIST) who have received prior treatment with 3 or more kinase inhibitor medicines, including imatinib, for their GIST.
It is not known if QINLOCK is safe and effective in children.

Before taking QINLOCK, tell your healthcare provider about all of your medical conditions, including if you:

- had a type of skin problem called palmar-plantar erythrodysesthesia syndrome
- have high blood pressure
- have heart problems
- had or plan to have surgery
- are pregnant or plan to become pregnant. QINLOCK can harm your unborn baby. Tell your healthcare provider if you or your partner becomes pregnant or you think you may be pregnant during treatment with QINLOCK.
  Females who are able to become pregnant:
  - Your healthcare provider will do a pregnancy test before you start treatment with QINLOCK.
  - You should use effective birth control (contraception) during treatment with QINLOCK and for 1 week after the last dose. Talk to your healthcare provider about birth control methods that may be right for you.
  Males with female partners who are able to become pregnant:
  - You should use effective birth control during treatment with QINLOCK and for at least 1 week after your final dose.
- are breastfeeding or plan to breastfeed. It is not known if QINLOCK passes into your breast milk. Do not breastfeed during treatment with QINLOCK and for at least 1 week after your final dose.

Tell your healthcare provider about all the medicines you take, including prescription and over-the-counter medicines, vitamins, and herbal supplements.
QINLOCK and certain other medicines can affect each other causing side effects or affect how QINLOCK works.
Know the medicines you take. Keep a list of them to show to your healthcare provider and pharmacist when you get a new medicine.

What should I avoid while taking QINLOCK?
Your skin may be sensitive to the sun or other forms of light (photosensitivity) during treatment with QINLOCK. Avoid or limit exposure to direct sunlight, sunlamps, and other sources of ultraviolet radiation during treatment and for at least 1 week after stopping treatment with QINLOCK. Use sunscreen and wear clothes that cover your skin if you need to be out in the sun.

How should I take QINLOCK?

- Take QINLOCK exactly as your healthcare provider tells you to.
- Your healthcare provider may temporarily or permanently stop treatment or change your dose of QINLOCK if you develop side effects during treatment.
- Do not change your dose or stop taking QINLOCK unless your healthcare provider tells you to.
- Take QINLOCK 1 time each day, at the same time each day.
- Take QINLOCK with or without food.
- Swallow QINLOCK tablets whole.
- If you vomit after taking a dose of QINLOCK, do not take an extra dose. Take your next dose of QINLOCK at your scheduled time.
- If you miss a dose of QINLOCK, take it as soon as you remember if it is within 8 hours of the scheduled dose. If more than 8 hours have passed, wait until your next scheduled dose.
- If you take more than the prescribed dose of QINLOCK, call your healthcare provider.

What are the possible side effects of QINLOCK?
QINLOCK may cause serious side effects, including:

- A skin problem called palmar-plantar erythrodysesthesia syndrome. Skin problems are common and sometimes can be severe. Tell your healthcare provider right away if you develop redness, pain, blisters, bleeding, or swelling on the palms of your hands or soles of your feet, or severe rash during treatment with QINLOCK.
- New skin cancers. QINLOCK may cause skin cancers called cutaneous squamous cell carcinoma, keratoacanthoma, or melanoma.
  Talk to your healthcare provider about your risk for these cancers. Your healthcare provider should check your skin before and during treatment with QINLOCK to look for any new skin cancers.
  Check your skin and tell your healthcare provider right away about any skin changes, including a:
  - new wart
  - skin sore or reddish bump that bleeds or does not heal
  - change in size or color of a mole
- High blood pressure (Hypertension). High blood pressure is common with QINLOCK and can be severe. Your healthcare provider should check your blood pressure regularly during treatment with QINLOCK.
- Heart problems. Your healthcare provider should check you for signs or symptoms of heart failure before starting QINLOCK and regularly during treatment with QINLOCK. Heart failure can be serious and can sometimes lead to death. Tell your healthcare provider right away if you have any of the following signs or symptoms during your treatment with QINLOCK:

- tiredness
- swelling of your stomach-area (abdomen), legs or ankles

- shortness of breath
- protruding neck veins

- Risk of wound healing problems. Wounds may not heal well during treatment with QINLOCK. Tell your healthcare provider if you plan to have any surgery before or during treatment with QINLOCK.
  - Your healthcare provider should tell you when to stop taking QINLOCK before a planned surgery.
  - Your healthcare provider should tell you when you may start taking QINLOCK again after surgery.
- Risk of sensitivity to sunlight (photosensitivity). See “What should I avoid while taking QINLOCK?”

The most common side effects of QINLOCK include:

- hair thinning or hair loss
- nausea
- constipation
- diarrhea
- vomiting

- tiredness
- stomach (abdominal) pain
- muscle pain
- decreased appetite

QINLOCK may affect fertility in males which may affect the ability to have children. Talk to your healthcare provider if this is a concern for you.
These are not all the possible side effects of QINLOCK.
Call your doctor for medical advice about side effects. You may report side effects to FDA at 1-800-FDA-1088.

How should I store QINLOCK?

- Store QINLOCK in the original container at room temperature between 68ºF to 77ºF (20ºC to 25ºC).
- QINLOCK comes with a desiccant packet in the bottle to protect your medicine from moisture. Do not remove the desiccant packet from the bottle.

Keep QINLOCK and all medicines out of the reach of children.

General information about the safe and effective use of QINLOCK.
Medicines are sometimes prescribed for purposes other than those listed in a Patient Information leaflet. Do not use QINLOCK for a condition for which it was not prescribed. Do not give QINLOCK to other people, even if they have the same symptoms that you have. It may harm them. You can ask your pharmacist or healthcare provider for information about QINLOCK that is written for health professionals.

What are the ingredients in QINLOCK?
Active ingredient: ripretinib
Inactive ingredients: crospovidone, hypromellose acetate succinate, lactose monohydrate, magnesium stearate, microcrystalline cellulose, and silicon dioxide
Manufactured for: Deciphera Pharmaceuticals, LLC, 200 Smith Street, Waltham, MA 02451
QINLOCK is a trademark of Deciphera, LLC. All other trademarks referenced herein are the property of their respective owners.
For more information, call 1-888-724-3274 or go to www.QINLOCK.com

This Patient Information has been approved by the U.S. Food and Drug Administration.

Revised: 10/2023

Principal Display Panel - 90 Tablet Carton Label

NDC: 73207-101-30 Rx only

QINLOCK™

(ripretinib) tablets

50 mg

Dispense the enclosed Patient
Information Leaflet to each patient.

90

TABLETS